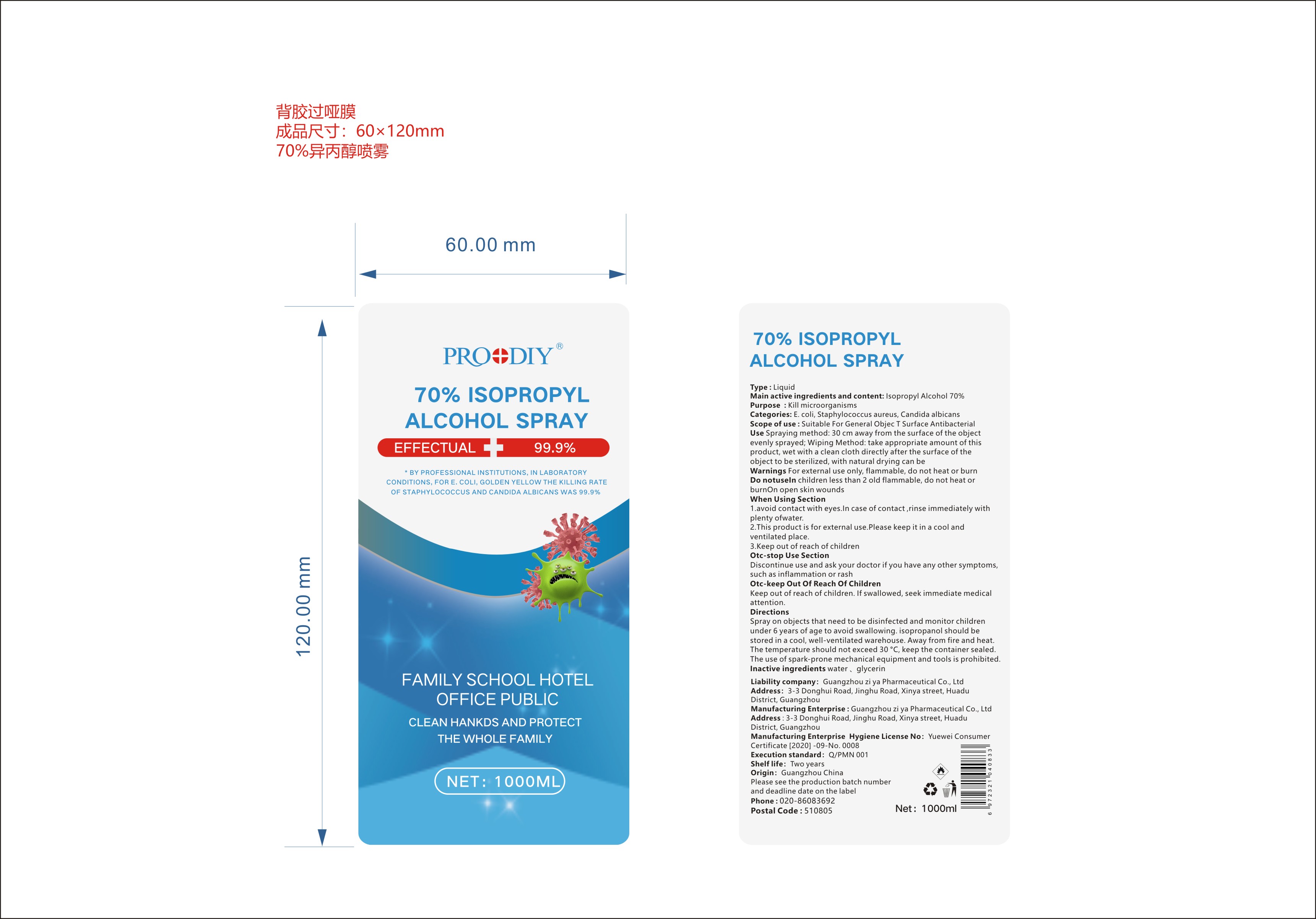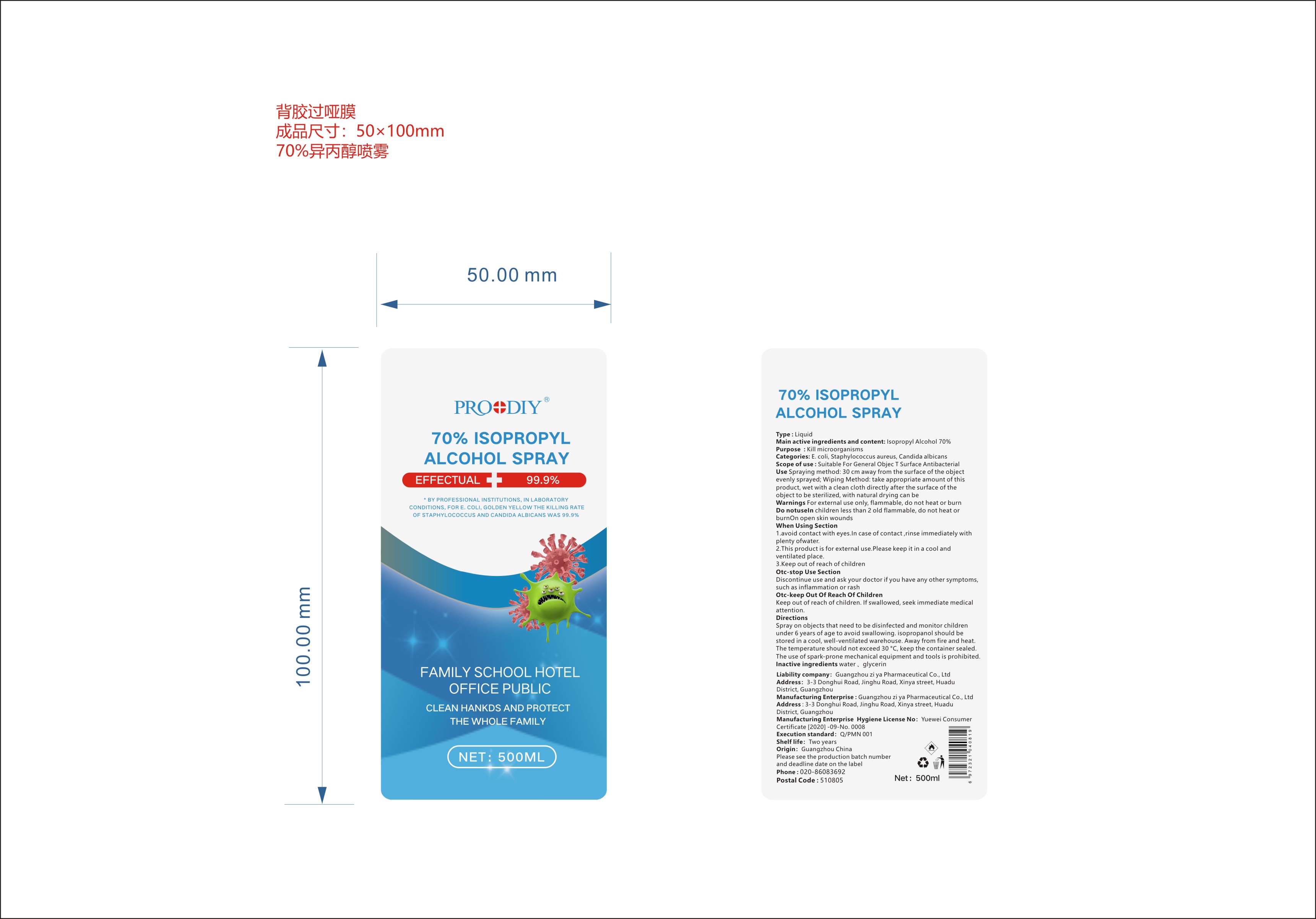 DRUG LABEL: 70% ISOPROPYL ALCOHOL
NDC: 79874-001 | Form: SPRAY
Manufacturer: Guangzhou Ziya Pharmaceutical Co., Ltd.
Category: otc | Type: HUMAN OTC DRUG LABEL
Date: 20200728

ACTIVE INGREDIENTS: ISOPROPYL ALCOHOL 70 mL/100 mL
INACTIVE INGREDIENTS: GLYCERIN; WATER

70% ISOPROPYL ALCOHOL SPRAY

Active Ingredient(s)

Isopropyl Alcohol 70%

Purpose

Kill microorganisms

Use

Use Spraying method: 30 cm away from the surface of the object evenly sprayed; Wiping Method: take appropriate amount of this product, wet with a clean cloth directly after the surface of the object to be sterilized, with natural drying can be

Warnings

Warnings For external use only, flammable, do not heat or burn

Do not use In children less than 2 old flammable, do not heat or burn On open skin wounds

WHEN USING

1. avoid contact with eyes. In case of contact rinse immediately with plenty ofwater.
2. This product is for external use. please keep it in a cool and ventilated place
3. Keep out of reach of children

STOP USE

Discontinue use and ask your doctor if you have any other symptoms,such as inflammation or rash

Keep out of reach of children. If swallowed, seek immediate medical attention

Directions

Spray on objects that need to be disinfected and monitor children under 6 years of age to avoid swallowing isopropanol should be stored in a cool, well-ventilated warehouse. away from fire and heat. The temperature should not exceed 30°C, keep the container sealed. The use of spark-prone mechanical equipment and tools is prohibited

Other information

Categories: E coli, Staphylo coccus aureus, Candida albicans

Scope of use: Suitable For General Objec T Surface Antibacterial

Inactive ingredients

water, glycerin